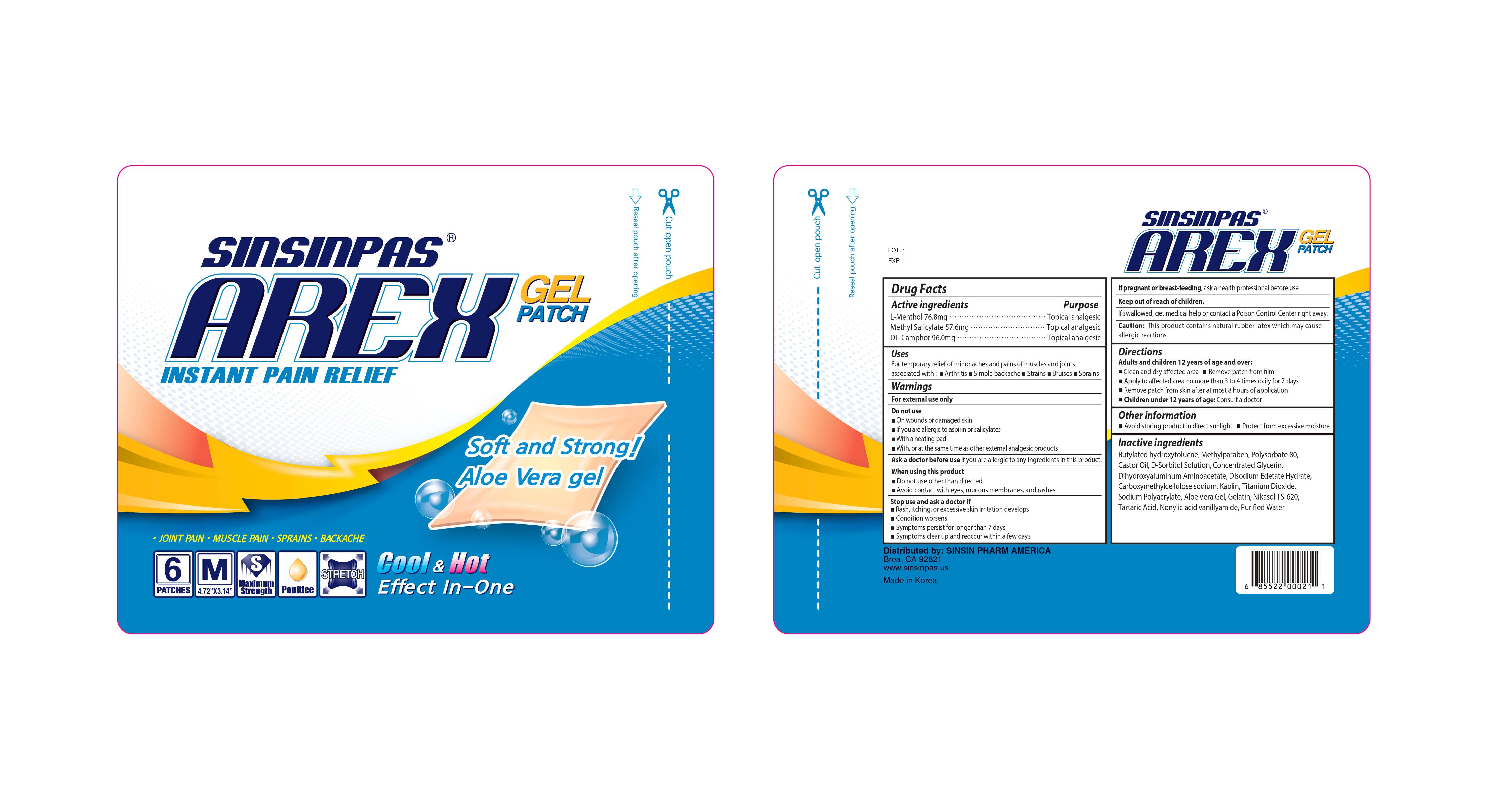 DRUG LABEL: SINSINPAS AREXGEL
NDC: 55264-114 | Form: PATCH
Manufacturer: Sinsin Pharmaceutical Co., Ltd.
Category: otc | Type: HUMAN OTC DRUG LABEL
Date: 20240105

ACTIVE INGREDIENTS: CAMPHOR (SYNTHETIC) 96 mg/1 1; LEVOMENTHOL 76.8 mg/1 1; METHYL SALICYLATE 57.6 mg/1 1
INACTIVE INGREDIENTS: CARBOXYMETHYLCELLULOSE SODIUM; NONIVAMIDE; SORBITOL; GELATIN; GLYCERYL MONOSTEARATE; EDETATE DISODIUM; ALUMINUM HYDROXIDE; KAOLIN; ALOE VERA LEAF; BUTYLATED HYDROXYTOLUENE; CASTOR OIL; WATER; TARTARIC ACID; TITANIUM DIOXIDE; METHYLPARABEN; POLYSORBATE 80; SODIUM POLYACRYLATE (8000 MW)

SINSINPAS AREX GEL PATCH

Active Ingredients

L-Menthol 76.8mg

Methyl Salicylate 57.6mg

DL-Camphor 96.0mg

Purpose

Topical Analgesic

Uses

For the temporarily relief of minor aches and pains of muscles and joints associated with:

- Arthritis
- Simple backache
- Strains
- Bruises
- Sprains

Warnings

For external use only

Do not use

- on wounds or damaged skin
- if you are allergic to any ingredients of this product
- with a heating pad
- with, or at the same time as, other external analgesic products

Ask a doctor before use if you are allergic to any ingredients in this product.

When using this product

- do not use other than directed
- avoid contact with eyes, mucous membranes, and rashes

Stop use and ask a doctor if

- rash, itching, or excessive skin irritation develops
- condition worsens
- symptoms persist for longer than 7 days
- symptoms clear up and reoccur within a few days

If pregnant or breast-feeding, ask a health professional before use.

Caution: This product contains natural rubber latex which may cause allergic reactions.

Keep out of reach of children

If swallowed, get medical help or contact a Poison Control Center (1-800-222-1222) right away.

Directions

Adults and children 12 years of age and over:

- Clean and dry affected area
- Remove patch from film
- Apply to affected area no more than 3 to 4 times daily for 7 days
- Remove patch from skin after at most 8 hours’ application

Children undress 12 years of age: consult a doctor

Other Information

- Avoid storing product in direct sunlight
- Protect from excessive moisture

Inactive Ingredients

Aloe vera gel, Butylated hydroxytoluene, Carboxymethylcellulose sodium, Castor oil, Concentrated glycerin, Disodium edetate hydrate, Dihydroxyalumium Aminoacetate, Gelatin, Kaolin, Methylparaben, Nonivamide, Polysorbate 80, Purified water, Sodium polyacrylate, Sorbitol, Tartaric acid, Titanium dioxide